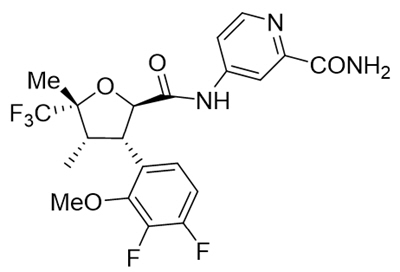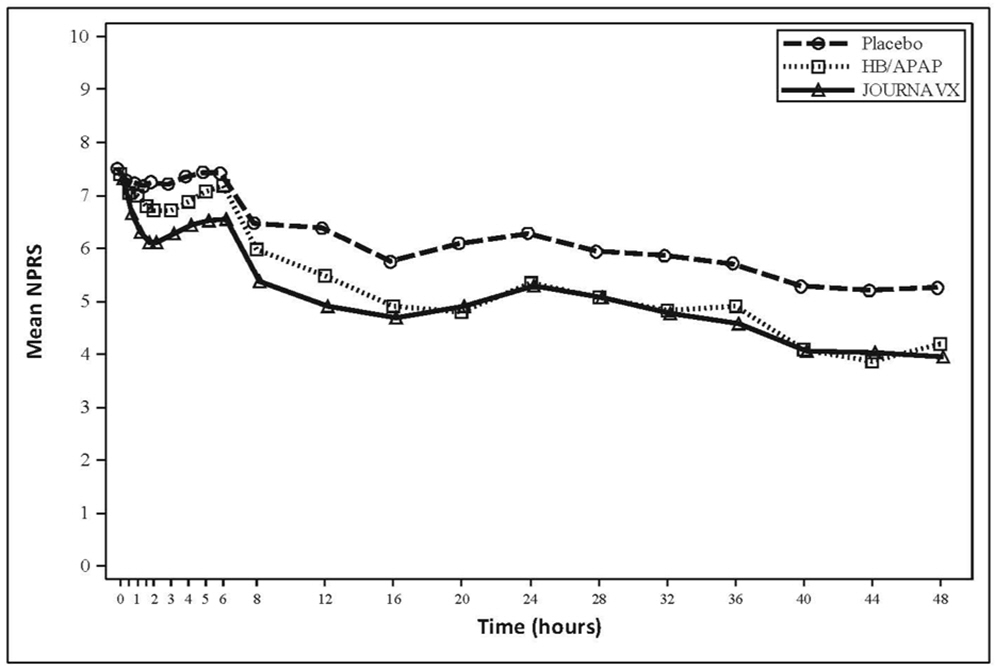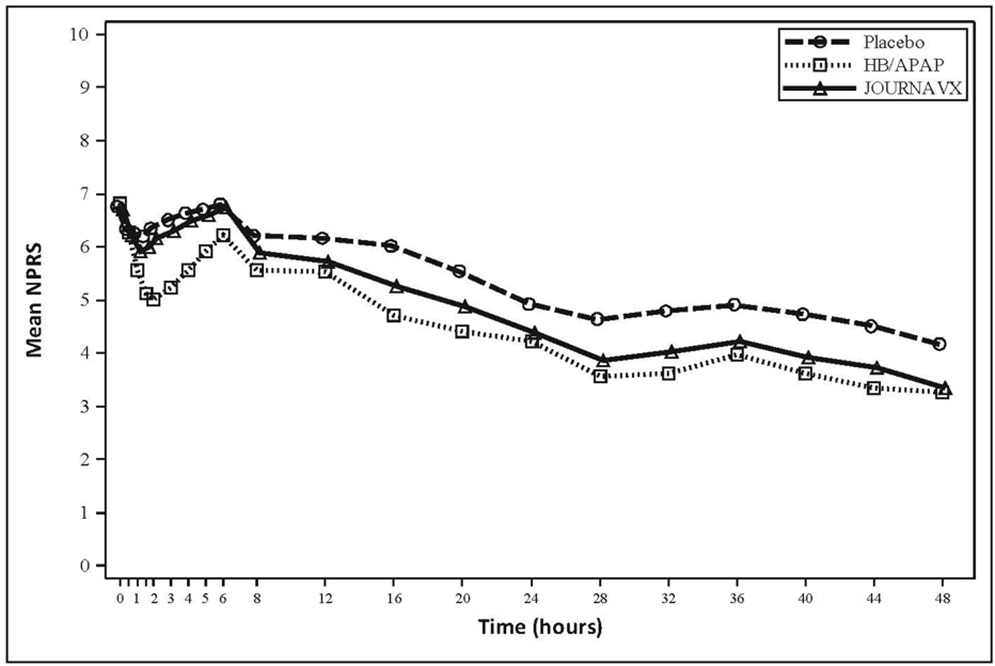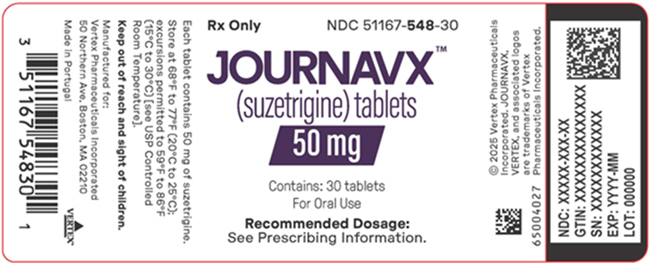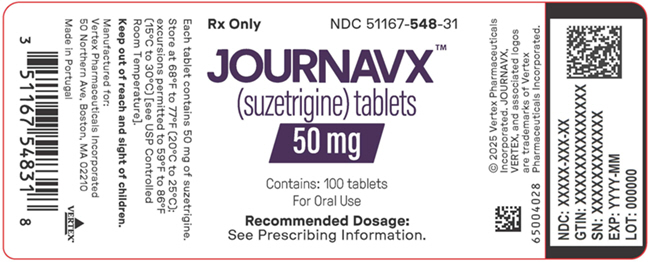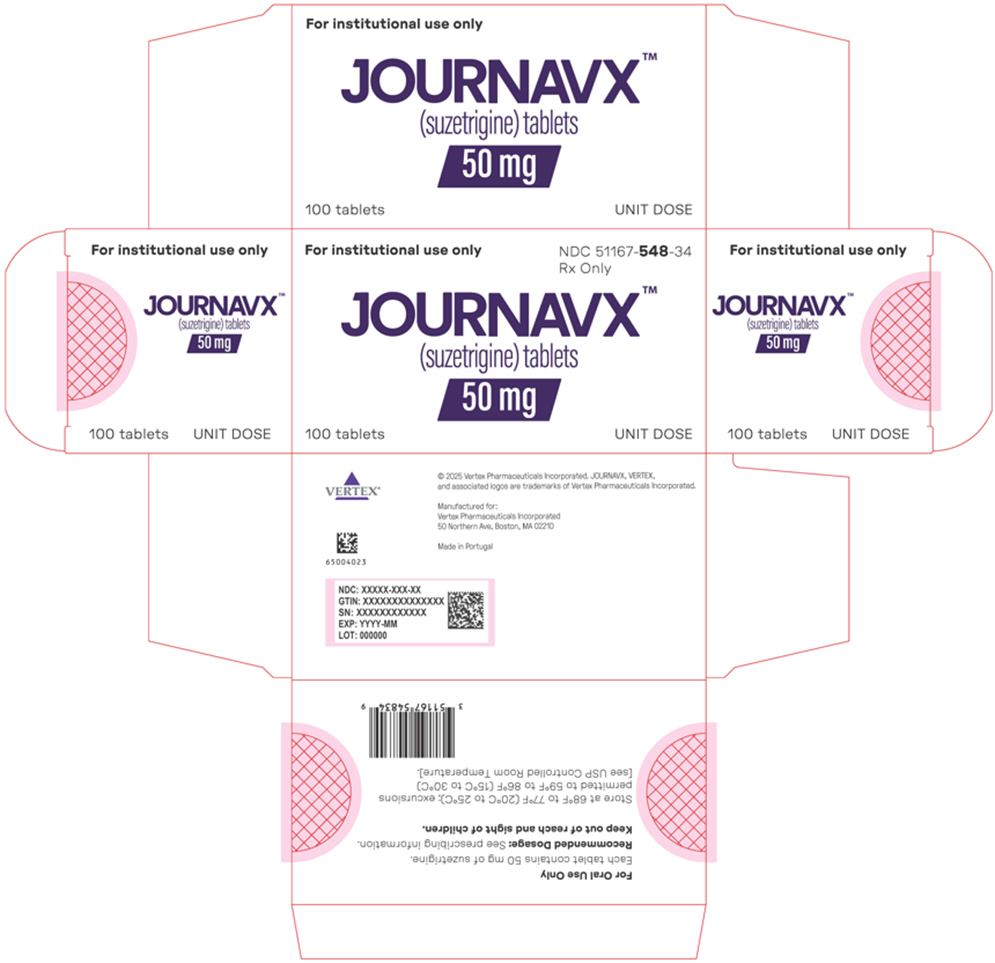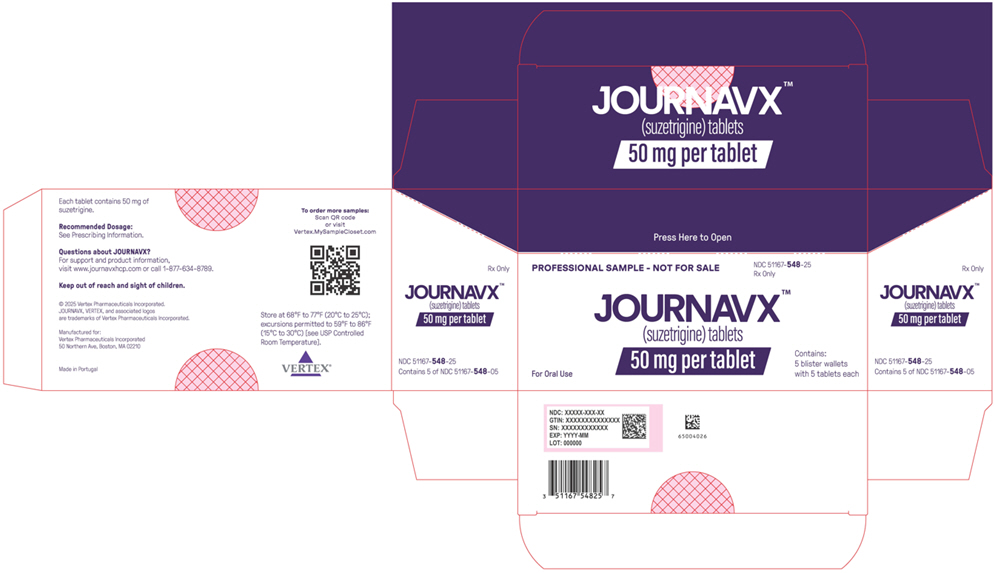 DRUG LABEL: JOURNAVX
NDC: 51167-548 | Form: TABLET, FILM COATED
Manufacturer: Vertex Pharmaceuticals Incorporated
Category: prescription | Type: HUMAN PRESCRIPTION DRUG LABEL
Date: 20260226

ACTIVE INGREDIENTS: Suzetrigine 50 mg/1 1
INACTIVE INGREDIENTS: HYPROMELLOSE ACETATE SUCCINATE, UNSPECIFIED; Microcrystalline cellulose; Croscarmellose sodium; Magnesium stearate; POLYVINYL ALCOHOL, UNSPECIFIED; Titanium dioxide; POLYETHYLENE GLYCOL 3350; Talc; FD&C BLUE NO. 2

HIGHLIGHTS OF PRESCRIBING INFORMATION

These highlights do not include all the information needed to use JOURNAVX safely and effectively. See full prescribing information for JOURNAVX.
JOURNAVX (suzetrigine) tablets, for oral use
Initial U.S. Approval: 2025

1 INDICATIONS AND USAGE

JOURNAVX is a sodium channel blocker indicated for the treatment of moderate to severe acute pain, including postoperative pain, in adults. (1)

2 DOSAGE AND ADMINISTRATION

- Swallow JOURNAVX tablets whole and do not chew or crush. (2.1)
- Recommended starting JOURNAVX oral dose is 100 mg. Take the starting dose on an empty stomach at least 1 hour before or 2 hours after food. Clear liquids may be consumed during this time (e.g., water, apple juice, vegetable broth, tea, black coffee). (2.1)
- Starting 12 hours after the starting dose, take 50 mg of JOURNAVX orally every 12 hours. Take these doses with or without food. (2.1)
- Use JOURNAVX for the shortest duration, consistent with individual patient treatment goals. Use of JOURNAVX for the treatment of acute pain has not been studied beyond 14 days. (2.1)
- See the full prescribing information for the recommended dosage in patients with hepatic impairment (2.2), for JOURNAVX dosage modifications with concomitant use of CYP3A inhibitors (2.3), and recommendations regarding missed dose(s). (2.4)
- Avoid food or drink containing grapefruit during treatment with JOURNAVX. (2.3)

3 DOSAGE FORMS AND STRENGTHS

Tablets: 50 mg (3)

4 CONTRAINDICATIONS

- Concomitant use with strong CYP3A inhibitors is contraindicated. (4)

5 WARNINGS AND PRECAUTIONS

Moderate and Severe Hepatic Impairment: Avoid use in patients with severe hepatic impairment (Child-Pugh Class C). Use in patients with moderate hepatic impairment may increase the risk of adverse reactions. The recommended dosage is lower in patients with moderate hepatic impairment (Child-Pugh Class B) than those with normal hepatic function. (5.4)

6 ADVERSE REACTIONS

The most common adverse reactions (greater incidence in JOURNAVX-treated patients compared to placebo-treated patients) were pruritus, muscle spasms, increased creatine phosphokinase, and rash. (6.1)

To report SUSPECTED ADVERSE REACTIONS, contact Vertex Pharmaceuticals Incorporated at 1-877-634-8789 or FDA at 1-800-FDA-1088 or www.fda.gov/medwatch.

7 DRUG INTERACTIONS

- Strong and Moderate CYP3A inhibitors: Concomitant use with strong CYP3A inhibitors is contraindicated. Reduce the JOURNAVX dose when used concomitantly with moderate CYP3A inhibitors. Avoid food or drink containing grapefruit. (2.3, 7.1, 12.3)
- Strong and Moderate CYP3A inducers: Avoid JOURNAVX use with strong or moderate CYP3A inducers. (7.1, 12.3)
- CYP3A substrates: If JOURNAVX is used concomitantly with sensitive CYP3A substrates or CYP3A substrates where minimal concentration changes may lead to loss of efficacy, refer to the Prescribing Information for the CYP3A substrates for dosing instructions. Dosage modification of the concomitant CYP3A substrates may be required when initiating or discontinuing JOURNAVX. (7.2, 12.3)
- Hormonal contraceptives: JOURNAVX-treated patients using hormonal contraceptives containing progestins other than levonorgestrel and norethindrone should use an additional nonhormonal contraceptive method or an alternative hormonal contraceptive during concomitant use and for 28 days after JOURNAVX discontinuation. (7.2)

FULL PRESCRIBING INFORMATION

1 INDICATIONS AND USAGE

JOURNAVX is indicated for the treatment of moderate to severe acute pain, including postoperative pain, in adults.

2 DOSAGE AND ADMINISTRATION

2.1 Recommended Dosage and Administration Instructions

Swallow JOURNAVX tablets whole and do not chew or crush.

The recommended starting dose of JOURNAVX is 100 mg orally. Take the starting dose on an empty stomach at least 1 hour before or 2 hours after food to avoid delay in onset of action [see Clinical Pharmacology (12.3)]. Clear liquids may be consumed during this time (e.g., water, apple juice, vegetable broth, tea, black coffee).

Starting 12 hours after the initial dose, take 50 mg of JOURNAVX orally every 12 hours. Take these doses with or without food [see Clinical Pharmacology (12.3)].

Avoid food or drink containing grapefruit during treatment with JOURNAVX [see Dosage and Administration (2.3)].

Use JOURNAVX for the shortest duration, consistent with individual patient treatment goals. Use of JOURNAVX for the treatment of moderate to severe acute pain has not been studied beyond 14 days.

2.2 Recommended Dosage in Patients with Hepatic Impairment

The recommended dosage of JOURNAVX in patients with hepatic impairment is described in Table 1.

Table 1: Recommended JOURNAVX Dosage in Patients with Hepatic Impairment
Degree of Hepatic Impairment (HI) | Recommended Dosage
Severe HI (Child-Pugh Class C) | Avoid use [see Use in Specific Populations (8.6)].
Moderate HI (Child-Pugh Class B) | Dose 1: The recommended starting dose of JOURNAVX is 100 mg taken orally. Take the starting dose on an empty stomach at least 1 hour before or 2 hours after food [see Clinical Pharmacology (12.3)]. Clear liquids may be consumed during this time (e.g., water, apple juice, vegetable broth, tea, black coffee). Doses 2, 3, and 4: Starting 12 hours after the initial dose, take 50 mg of JOURNAVX orally every 12 hours. Take these doses with or without food [see Clinical Pharmacology (12.3)]. Dose 5 and Subsequent Doses: Starting 12 hours after Dose 4, take 50 mg of JOURNAVX orally every 24 hours. Take these dose(s) with or without food [see Clinical Pharmacology (12.3)].
Mild HI (Child-Pugh Class A) | The recommended dosage is the same as in those with normal hepatic function [see Dosage and Administration (2.1)].

2.3 Dosage Modifications for CYP3A Inhibitors

JOURNAVX is contraindicated in patients taking strong CYP3A inhibitors. When JOURNAVX is administered to patients taking moderate CYP3A inhibitors reduce the JOURNAVX dose, as described below:

Dose 1: The recommended starting dose of JOURNAVX is 100 mg orally. Take the starting dose on an empty stomach at least 1 hour before or 2 hours after food [see Clinical Pharmacology (12.3)]. Clear liquids may be consumed during this time (e.g., water, apple juice, vegetable broth, tea, black coffee).

Doses 2, 3, and 4: Starting 12 hours after the initial dose, take 50 mg of JOURNAVX orally every 12 hours. Take these doses with or without food [see Clinical Pharmacology (12.3)].

Dose 5 and Subsequent Doses: Starting 12 hours after Dose 4, take 50 mg of JOURNAVX orally every 24 hours. Take these dose(s) with or without food [see Clinical Pharmacology (12.3)].

Avoid food or drink containing grapefruit during treatment with JOURNAVX [see Drug Interactions (7.1), Clinical Pharmacology (12.3)].

2.4 Recommendations Regarding Missed Dose(s)

For patients on the standard recommended dosing schedule [see Dosage and Administration (2.1)]:

- If a dose is missed, take the missed dose as soon as possible and then take the next scheduled dose at the recommended time.
- If two or more doses are missed, take 100 mg and then take the next scheduled dose at the recommended time.

For patients with moderate hepatic impairment or patients taking moderate CYP3A inhibitors [see Dosage and Administration (2.2, 2.3)], if a dose is missed, take the missed dose as soon as possible. If the next scheduled dose is within 6 hours, skip the next scheduled dose, and take the subsequent doses at the recommended time.

3 DOSAGE FORMS AND STRENGTHS

Tablets: 50 mg, blue, film-coated, oblong tablets debossed with "VX50" on one side and plain on the other.

4 CONTRAINDICATIONS

Concomitant use of JOURNAVX with strong CYP3A inhibitors is contraindicated [see Warnings and Precautions (5.1), Drug Interactions (7.1)].

5 WARNINGS AND PRECAUTIONS

5.1 Increased Risk of Adverse Reactions with Concomitant Use with Strong or Moderate CYP3A Inhibitors

Strong and moderate CYP3A inhibitors increase suzetrigine and M6-SUZ (active metabolite) exposures which may cause JOURNAVX adverse reactions. Concomitant use of JOURNAVX with strong CYP3A inhibitors is contraindicated [see Drug Interactions (7.1), Clinical Pharmacology (12.3)]. Reduce the JOURNAVX dosage with moderate CYP3A inhibitors [see Dosage and Administration (2.3)].

5.2 Risk of Drug Interactions with Certain CYP3A Substrates

Suzetrigine is an inducer of CYP3A. If JOURNAVX is used concomitantly with sensitive CYP3A substrates or CYP3A substrates where minimal concentration changes may lead to loss of efficacy, refer to the Prescribing Information for the CYP3A substrates for dosing instructions. Dosage adjustment of the concomitant CYP3A substrates may be required when initiating or discontinuing JOURNAVX [see Drug Interactions (7.2), Clinical Pharmacology (12.3)].

5.3 Risk of Drug Interactions with Certain Hormonal Contraceptives

JOURNAVX-treated patients taking concomitant hormonal contraceptives containing progestins other than levonorgestrel and norethindrone should use additional nonhormonal contraceptives (such as condoms) or use alternative contraceptives (e.g., a combined oral contraceptive containing ethinyl estradiol as the estrogen and levonorgestrel or norethindrone as the progestin, an intrauterine system) during JOURNAVX treatment and for 28 days after discontinuation of JOURNAVX [see Drug Interactions (7.2), Clinical Pharmacology (12.3)].

5.4 Risk of Adverse Reactions in Patients with Moderate and Severe Hepatic Impairment

Patients with moderate hepatic impairment have higher systemic exposures of suzetrigine and M6-SUZ (active metabolite) than those with normal hepatic function which may increase the risk of JOURNAVX related adverse reactions [see Use in Specific Populations (8.6), Clinical Pharmacology (12.3)].

Avoid use of JOURNAVX in patients with severe hepatic impairment (Child-Pugh Class C). The recommended JOURNAVX dosage is lower in patients with moderate hepatic impairment (Child-Pugh Class B) than those with normal hepatic function [see Dosage and Administration (2.2)].

6 ADVERSE REACTIONS

6.1 Clinical Trials Experience

Because clinical trials are conducted under widely varying conditions, adverse reaction rates observed in the clinical trials of a drug cannot be directly compared to rates in the clinical trials of another drug and may not reflect the rates observed in practice.

The safety profile of JOURNAVX is primarily based on data from the pooled, double-blind, placebo- and active-controlled trials in 874 adult patients with moderate to severe acute pain following full abdominoplasty (Trial 1) and bunionectomy (Trial 2) [see Clinical Studies (14)], with supportive safety data from one single arm trial in 256 adult patients with moderate to severe acute pain in a broad range of acute pain conditions (Trial 3).

In Trials 1 and 2, 874 patients received at least one dose of JOURNAVX. The proportion of patients in Trials 1 and 2 who discontinued study drug prematurely due to adverse events was:

- 0.6% in JOURNAVX-treated patients (postprocedural hematoma [0.2%], hypotension [0.2%], syncope [0.1%]),
- 0.6% in hydrocodone bitartrate/acetaminophen (HB/APAP)-treated patients (hypotension/orthostatic hypotension [0.2%], migraine [0.1%], intra-abdominal hematoma [0.1%], nausea [0.1%], pyrexia [0.1%]), and
- 0.2% in placebo-treated patients (hypotension [0.2%], tachycardia [0.2%]).

The safety profile of JOURNAVX was also evaluated by the following subgroup analyses: age (≥ 18 to < 65 years and ≥ 65 years), sex, and race. Since most patients enrolled in the clinical trials were ≥ 18 to < 65 years of age, female, and white, there was insufficient data to detect differences in safety signals between these subgroups.

Table 2 displays adverse reactions that occurred more frequently in JOURNAVX-treated patients than placebo-treated patients in the pooled Trials 1 and 2.

Table 2: Adverse Reactions Reported in ≥1% of JOURNAVX-Treated Patients and Greater than Rate of Placebo in Two 48-hour Trials in Moderate to Severe Acute Pain (Trials 1 and 2, Pooled)
Adverse Reactions (Preferred Term) | Placebo (N = 438) n (%) | JOURNAVX (N = 874) n (%) | HB/APAP [Patients received 5 mg/325 mg of oral hydrocodone bitartrate/acetaminophen (HB/APAP) every 6 hours.] (N = 879) n (%)
Pruritus | 7 (1.6) | 18 (2.1) | 30 (3.4)
Muscle spasms | 2 (0.5) | 11 (1.3) | 6 (0.7)
Increased blood creatine phosphokinase | 2 (0.5) | 10 (1.1) | 7 (0.8)
Rash | 2 (0.5) | 10 (1.1) | 6 (0.7)

Nausea and Vomiting

In Trial 1, the incidence of patients who experienced either nausea or vomiting was 20% in JOURNAVX-treated patients, 33% in HB/APAP-treated patients, and 25% in placebo-treated patients. In Trial 2, the incidence of patients who experienced either nausea or vomiting was 9% in JOURNAVX-treated patients, 16% in HB/APAP-treated patients, and 12% in placebo-treated patients.

Laboratory Abnormalities

Creatine Phosphokinase Elevations: In Trials 1 and 2, 2.9% of JOURNAVX-treated patients and 1.2% of placebo-treated patients had a creatine phosphokinase (CPK) level > 3 times the upper limit of normal. The incidence of increased blood CPK was 1.1% in JOURNAVX-treated patients and 0.5% in placebo-treated patients. All reports of CPK elevations occurred in the post-surgical setting. There were no associated signs or symptoms, no serious adverse reactions, and no patients required treatment discontinuation or interruption.

Decreased Estimated Glomerular Filtration Rate: In Trials 1 and 2, 2.5% of JOURNAVX-treated patients and 0.9% of placebo-treated patients had a decrease in estimated glomerular filtration rate (eGFR) of ≥ 25% but < 50%. Follow-up eGFR data for these controlled trials was not available after treatment discontinuation. Similar decreases in eGFR also occurred in Trial 3 (the open-label Phase 3 study) and appeared to resolve to baseline by the final safety follow-up visit. There was no control arm for comparison. There were no adverse reactions of eGFR decrease in JOURNAVX-treated patients.

Adverse Reactions from the Open-Label Study (Trial 3)

In an open-label study of patients with moderate to severe acute pain following a surgical procedure or nonsurgical condition [NCT05661734], a total of 256 adult patients received at least one dose of JOURNAVX. Patients received 100 mg as a first dose, then 50 mg every 12 hours and continued to receive JOURNAVX for up to 14 days or until their pain resolved. Rescue medication of 650 mg of acetaminophen and 400 mg of ibuprofen together every 6 hours was permitted as needed for pain relief. The patients' perceptions of pain control was captured by patient global assessment (PGA). The mean duration of treatment with JOURNAVX was 9.6 days. The majority of patients were female (68%), and the median age was 43 years (range: 18 to 78).

In Trial 3, a total of 222 (87%) patients received JOURNAVX for post-surgical pain; orthopedic surgery was the most common (e.g., ligament operation, arthrodesis), followed by plastic surgery (e.g., liposuction, mammoplasty), otorhinolaryngologic surgery (e.g., nasal septal operation, turbinoplasty), and general and urologic surgery (e.g., inguinal hernia repair). Thirty-four (13%) patients received JOURNAVX for non-surgical pain (e.g., arthralgias, limb pain, and sprains/strains).

The proportion of patients who discontinued study drug prematurely was 2% due to adverse events (arrhythmia [0.4%], nausea [0.4%], somnolence [0.4%], rash [0.4%]) and 1.6% due to lack of efficacy.

The safety profile of JOURNAVX in Trial 3 was consistent with that observed in Trials 1 and 2.

7 DRUG INTERACTIONS

7.1 Effect of Other Drugs on JOURNAVX

Table 3 describes drug interactions where concomitant use of another drug affects the use of JOURNAVX.

Table 3: Drug Interactions: Concomitant Use of Other Drugs that Affect the Use of JOURNAVX
Strong and Moderate [Food or drink containing grapefruit should be avoided during treatment with JOURNAVX.] CYP3A Inhibitors
Prevention or Management | Strong CYP3A inhibitors: Concomitant use of JOURNAVX with strong CYP3A inhibitors is contraindicated [see Warnings and Precautions (5.1)].
Prevention or Management | Moderate CYP3A inhibitors: Reduce the JOURNAVX dosage [see Dosage and Administration (2.3), Warnings and Precautions (5.1)].
Mechanism and Clinical Effect(s) | Suzetrigine and M6-SUZ are CYP3A substrates. Strong and moderate CYP3A inhibitors increase suzetrigine and M6-SUZ (active metabolite of suzetrigine) exposures [see Clinical Pharmacology (12.3)], which may cause JOURNAVX adverse reactions.
Strong and Moderate CYP3A Inducers
Prevention or Management | Avoid concomitant use of JOURNAVX with strong and moderate CYP3A inducers.
Mechanism and Clinical Effect(s) | Suzetrigine and M6-SUZ are CYP3A substrates. Concomitant use of strong or moderate CYP3A inducers results in reduced exposures of suzetrigine and M6-SUZ, which may result in reduced JOURNAVX efficacy [see Clinical Pharmacology (12.3)].

7.2 Effect of JOURNAVX on Other Drugs

CYP3A Substrates

If JOURNAVX is used concomitantly with sensitive CYP3A substrates or CYP3A substrates where minimal concentration changes may lead to loss of efficacy, refer to the Prescribing Information for the CYP3A substrates for dosing instructions. Dosage modification of the concomitant CYP3A substrates may be required when initiating or discontinuing JOURNAVX [see Warnings and Precautions (5.2)].

Suzetrigine is an inducer of CYP3A. Concomitant use with JOURNAVX may reduce the exposure of sensitive CYP3A substrates which may decrease the efficacy of these substrates. Discontinuation of JOURNAVX may increase the exposure of sensitive CYP3A substrates [see Warnings and Precautions (5.2), Clinical Pharmacology (12.3)].

Hormonal Contraceptives

JOURNAVX-treated patients using hormonal contraceptives containing progestins other than levonorgestrel and norethindrone should use additional nonhormonal contraceptives (such as condoms), or use alternative contraceptives (such as a combined oral contraceptive containing ethinyl estradiol as the estrogen and levonorgestrel or norethindrone as the progestin, or an intrauterine system) during treatment with JOURNAVX and for 28 days after discontinuation of JOURNAVX [see Warnings and Precautions (5.3)].

JOURNAVX did not result in clinically significant changes in the pharmacokinetics of ethinyl estradiol and levonorgestrel when used concomitantly with an oral contraceptive containing ethinyl estradiol and levonorgestrel [see Clinical Pharmacology (12.3)].

8 USE IN SPECIFIC POPULATIONS

8.1 Pregnancy

Risk Summary

There are no available data on the use of JOURNAVX during pregnancy to evaluate for a drug-associated risk of major birth defects, miscarriage or other adverse maternal or fetal outcomes.

In animal reproduction studies in rats, effects on implantation and maintenance of pregnancy occurred at oral suzetrigine doses of ≥ 2.2-times the maximum recommended human dose (MRHD) when administered during early embryonic development or throughout organogenesis. In a pre- and postnatal development study, reduced mean gestation length and increased postnatal pup mortality were observed at maternal rat exposures of 1.6-times the MRHD and decreased rat pup body weights were observed during the period of birth to weaning at maternal exposures of 2.2-times the MRHD. No malformations were observed when suzetrigine was administered orally to rats and rabbits during the period of organogenesis at doses up to 2.2- and 5.9-times, respectively, the MRHD. The clinical relevance of these findings is unclear.

The background risk of major birth defects and miscarriage in patients with moderate to severe acute pain is unknown. All pregnancies have a background risk of birth defect, loss, or other adverse outcomes. In the U.S. general population, the estimated background risk of major birth defects and miscarriage in clinically recognized pregnancies is 2% to 4% and 15% to 20%, respectively.

Data

Animal Data

Suzetrigine was administered orally to pregnant rabbits during the period of organogenesis at 50, 100, and 200 mg/kg/day (approximately 1.6-, 3.1-, and 5.9-times, respectively, the steady state MRHD exposure based on AUC). Increased post-implantation loss and lower fetal body weight were observed at 200 mg/kg/day, which is a dose that also caused maternal toxicity. No adverse embryofetal effects were observed at doses up to 100 mg/kg.

Suzetrigine was administered orally to pregnant rats during the period of organogenesis at 5, 10, and 15 mg/kg/day (approximately 0.57-, 1.6-, and 2.2-times, respectively, the steady state MRHD exposure based on AUC). Increased post-implantation loss and lower number of live fetuses were observed at 15 mg/kg/day. No adverse embryofetal effects were observed at doses up to 10 mg/kg. Placental transfer of suzetrigine was observed in pregnant rats.

In a pre- and postnatal development study, suzetrigine was administered orally to pregnant rats at doses of 5, 10, and 15 mg/kg/day (approximately 0.57-, 1.6-, and 2.2-times, respectively, the steady state MRHD exposure based on AUC) from Gestation Day 6 through Lactation Day 20. Reduced mean gestation length and increased postnatal pup mortality between birth and Postnatal Day 4 were observed at ≥ 10 mg/kg and increased incidences of fully resorbed litters, lower live newborn pups, and reductions in pup body weights were observed at 15 mg/kg. No effects on learning and memory or sexual maturation were observed at dose up to 15 mg/kg/day.

The effects on implantation, maintenance of pregnancy, reduced mean gestation length, and increased postnatal pup mortality in rats are of uncertain relevance to humans.

8.2 Lactation

Risk Summary

There are no data on the presence of suzetrigine or its metabolites in human milk, the effects on the breastfed infant, or the effects on milk production. Suzetrigine is present in animal milk. When a drug is present in animal milk, it is likely that the drug will be present in human milk. The developmental and health benefits of breastfeeding should be considered along with the mother's clinical need for JOURNAVX and any potential adverse effects on the breastfed child from JOURNAVX or from the underlying maternal condition.

8.3 Females and Males of Reproductive Potential

Contraception

Advise patients using hormonal contraceptives containing progestins other than levonorgestrel and norethindrone to use an additional nonhormonal contraceptive or to use alternative contraceptives during JOURNAVX treatment and for 28 days after discontinuation of JOURNAVX [see Drug Interactions (7.2)].

Infertility

In a female fertility study in rats, increased pre-implantation loss was observed at oral suzetrigine doses of ≥ 2.2-times the MRHD when administered prior to mating and through Gestation Day 7. Following discontinuation of suzetrigine for 4 weeks, the increased pre-implantation loss in rats was not observed. The finding in rats may be explained by the effect of suzetrigine on the rat progesterone receptor, which was more sensitive to suzetrigine than the human progesterone receptor based on in vitro studies. The finding in the rat study is of uncertain relevance to humans.

JOURNAVX may reversibly impact the likelihood of females of reproductive potential to become pregnant while on treatment. Patients using contraceptives should continue to use contraceptives [see Nonclinical Toxicology (13.1)].

8.4 Pediatric Use

The safety and effectiveness of JOURNAVX has not been established in pediatric patients.

8.5 Geriatric Use

Of the total 1130 patients with moderate to severe acute pain who received JOURNAVX in the Phase 3 studies [see Clinical Studies (14)], 71 patients (6.3%) were 65 years of age and older.

Clinical studies of JOURNAVX did not include sufficient numbers of patients aged 65 years and older to determine whether they respond differently from younger patients. However, based on population pharmacokinetic analyses in patients with ages ranging from 18 to 75 years, age does not have a clinically relevant impact on suzetrigine exposure [see Clinical Pharmacology (12.3)].

8.6 Hepatic Impairment

JOURNAVX has not been studied in patients with severe hepatic impairment. Avoid use of JOURNAVX in patients with severe hepatic impairment (Child-Pugh Class C) [see Warnings and Precautions (5.4)]. The recommended JOURNAVX dosage is lower in patients with moderate hepatic impairment (Child-Pugh Class B) [see Dosage and Administration (2.2)] than those with normal hepatic function. The recommended dosage in patients with mild hepatic impairment (Child-Pugh Class A) is the same as those with normal hepatic function.

Patients with moderate hepatic impairment had greater suzetrigine and M6-SUZ (the active metabolite) exposure than those with normal hepatic function [see Clinical Pharmacology (12.3)], which may increase the risk of suzetrigine adverse reactions.

8.7 Renal Impairment

JOURNAVX has not been studied in patients with renal impairment of eGFR < 15 mL/min. Avoid use of JOURNAVX in patients with renal impairment of eGFR < 15 mL/min [see Clinical Pharmacology (12.3)]. The recommended dosage in patients with eGFR > 15 mL/min is the same as those with normal kidney function.

10 OVERDOSAGE

No specific antidote is available for overdose with JOURNAVX. Treatment of overdose consists of general supportive measures including monitoring of vital signs and observation of the clinical status of the patient. Consider contacting the Poison Help line (1-800-222-1222) or a medical toxicologist for additional overdose management recommendations.

11 DESCRIPTION

The active ingredient in JOURNAVX (suzetrigine) tablets is suzetrigine, a sodium channel blocker, which has the following chemical name:

4-[(2R,3S,4S,5R)-3-(3,4-difluoro-2-methoxyphenyl)-4,5-dimethyl-5-(trifluoromethyl)oxolane-2-amido]pyridine-2-carboxamide. Its molecular formula is C21H20F5N3O4.

Suzetrigine's molecular weight is 473.39 g/mol. Suzetrigine has the following structural formula:

Suzetrigine is a white to off-white solid and is practically insoluble in water.

JOURNAVX is available as a blue, film-coated tablet for oral administration containing 50 mg of suzetrigine and the following inactive ingredients: croscarmellose sodium, hypromellose acetate succinate, magnesium stearate, and microcrystalline cellulose. The tablet film coat contains FD&C Blue #2 aluminum lake, polyethylene glycol, polyvinyl alcohol-partially hydrolyzed, talc, and titanium dioxide.

12 CLINICAL PHARMACOLOGY

12.1 Mechanism of Action

Suzetrigine is a selective blocker of the NaV1.8 voltage-gated sodium channel, compared to other known voltage-gated sodium channels (NaV1.1 through 1.9). NaV1.8 is expressed in peripheral sensory neurons including dorsal root ganglion neurons, where its role is to transmit pain signals (action potentials). By selectively inhibiting NaV1.8 channels, suzetrigine inhibits transmission of pain signals to the spinal cord and brain. M6-SUZ, a major active metabolite, is a less potent inhibitor of NaV1.8 than suzetrigine by 3.7-fold.

12.2 Pharmacodynamics

Cardiac Electrophysiology

At 2 times the exposure of the maximum recommended JOURNAVX dose, clinically significant QTc prolongation was not observed.

12.3 Pharmacokinetics

The pharmacokinetic parameters for suzetrigine and its major active metabolite, M6-SUZ, are shown in Table 4.

Table 4: Pharmacokinetic Parameters of Suzetrigine and M6-SUZ
 | Suzetrigine | M6-SUZ (Active Metabolite) [Based on an in vitro electrophysiology assay in human dorsal root ganglion neurons, M6-SUZ is a less potent inhibitor of NaV1.8 than suzetrigine by 3.7-fold.]
General Information
Steady State AUC0-24h (CV%), µg*h/mL | 11.5 (25.6%) | 34.7 (25.6%)
Steady State Cmax (CV%), µg/mL | 0.62 (27.7%) | 1.5 (24.5%)
Time to 90% Steady State, days | 3 | 5
Mean (CV%) Accumulation Ratio [Based on simulations of a dose of 50 mg every 12 hours (q12h).] | 3.4 (30.2%) | 4.5 (30.6%)
Absorption
Median Tmax (range), hours | 3.0 hours (1.50, 5.03) | 10.0 hours (4.0, 48.1)
Distribution [Suzetrigine and M6-SUZ do not partition preferentially into human red blood cells.]
Mean (CV%) Apparent Volume of Distribution, L | 495 (25.0%) | NA
Protein Binding | 99% | 96%
Elimination
Mean (CV%) Effective Half-Life, hours | 23.6 (36.2%) | 33.0 (34.9%)
Steady State Mean (CV%) Apparent Oral Clearance, L/hours | 13.9 (37.5%) | NA
Metabolism
Primary Pathway | CYP3A | CYP3A
Excretion
Primary Pathway | - Feces: 49.9% (9.1% SUZ and rest as metabolites) - Urine: 44.0% (primarily as metabolites)
AUC: area under the concentration versus time curve; CV: coefficient of variation; Cmax: maximum observed concentration; Tmax: time of maximum concentration; NA: not applicable

Effect of Food

Administration of 100 mg of JOURNAVX (the first dose) with a high-fat meal (800 to 1000 calories, 50% derived from fat), a moderate-fat meal (600 calories, 30% derived from fat), and a low-fat meal (up to 500 calories with no more than 25% derived from fat) resulted in decreased initial concentrations of suzetrigine and M6-SUZ in comparison to a fasted state. The median Tmax of suzetrigine and M6-SUZ in the fasted state was 3 hours and 8 to 10 hours, respectively. When administered in the fed state (high-fat meal or moderate-fat meal) the median Tmax of suzetrigine was delayed to 5 hours and the median Tmax of M6-SUZ was delayed to 24 hours. The Cmax and AUC of suzetrigine and M6-SUZ were not affected by any of the meal conditions, including a high-fat meal consumed one hour after JOURNAVX administration.

Administration of the second JOURNAVX dose of 50 mg with or without regard to meals is predicted to not affect the systemic exposures of suzetrigine and M6-SUZ.

Specific Populations

No clinically significant differences in pharmacokinetics of suzetrigine and M6-SUZ were observed based on age (18-75 years), sex, body weight (44-126 kg), race, and renal impairment (eGFR ≥ 15 mL/min by CKD-EPI equation with adjustment for the body surface area). The effect of renal impairment with eGFR < 15 mL/min on suzetrigine and M6-SUZ pharmacokinetics is unknown.

Patients with Hepatic Impairment

In patients with mild hepatic impairment (Child-Pugh Class A), no clinically significant differences in pharmacokinetics of suzetrigine and M6-SUZ were observed. In patients with moderate hepatic impairment (Child-Pugh Class B), at steady state, suzetrigine AUC0-12h increased by 1.5-fold (90% CI: 1.1-2.1) and Cmax increased by 1.3-fold (90% CI: 1.0-1.7) and M6-SUZ AUC0-12h and Cmax both increased by 1.2-fold (AUC 90% CI: 0.83-1.6; Cmax 90% CI: 0.84-1.6). The effect of severe hepatic impairment (Child-Pugh Class C) on suzetrigine and M6-SUZ pharmacokinetics is unknown.

Drug Interaction Studies

Clinical Studies and Model-Informed Approaches

Strong CYP3A Inhibitors: Concomitant administration of itraconazole (a strong CYP3A inhibitor) with a single dose of JOURNAVX increased the geometric mean (90% CI) AUC0-inf of suzetrigine and M6-SUZ by 4.8-fold (4.3-5.4) and 4.4-fold (3.6-5.4), respectively, while the geometric mean (90% CI) Cmax of suzetrigine increased by 1.5-fold (1.3-1.6) and Cmax of M6-SUZ decreased by 32% (24-39%) [see Drug Interactions (7.1)].

Moderate CYP3A Inhibitors: Concomitant administration of fluconazole (a moderate CYP3A inhibitor) with JOURNAVX with the recommended dosage modification [see Dosage and Administration (2.3)] is predicted to increase the geometric mean (90% CI) AUCtau of suzetrigine and M6-SUZ by 1.5-fold (1.4-1.5) and 1.2-fold (1.2-1.3), respectively, while the geometric mean (90% CI) Cmax of suzetrigine and M6-SUZ is predicted to increase by 1.4-fold (1.4-1.5) and 1.1-fold (1.1-1.2), respectively, when compared to the regular recommended dosage in the absence of fluconazole [see Dosage and Administration (2.3), Drug Interactions (7.1)].

Strong CYP3A Inducers: Concomitant administration of rifampin (strong CYP3A inducer) at steady state with a single dose of JOURNAVX decreased the geometric mean (90% CI) AUC0-inf of suzetrigine and M6-SUZ by 93% (91-94%) and 85% (83-86%), respectively, while the geometric mean (90% CI) Cmax of suzetrigine decreased by 80% (75-83%) and the Cmax of M6-SUZ increased by 1.3-fold (1.1-1.5) [see Drug Interactions (7.1)].

Moderate CYP3A Inducers: Concomitant administration of efavirenz (moderate CYP3A inducer) with a single dose of JOURNAVX is predicted to decrease the geometric mean (90% CI) AUC0-t of suzetrigine and M6-SUZ by 63% (61-65%) and 60% (58-62%), respectively, while the geometric mean (90% CI) Cmax of suzetrigine is predicted to decrease by 29% (27-32%) and M6-SUZ is predicted to increase by 1.3-fold (1.3-1.4), respectively [see Drug Interactions (7.1)].

Sensitive CYP3A Substrates: JOURNAVX administered 50 mg every 12 hours, at steady state decreased the geometric mean (90% CI) AUC0-inf of midazolam (sensitive CYP3A substrate) by 48% (43-53%) and Cmax by 37% (27-45%) [see Drug Interactions (7.2)].

Proton Pump Inhibitors: No clinically significant differences in suzetrigine and M6-SUZ pharmacokinetics were observed when JOURNAVX was used concomitantly with omeprazole.

Other Drugs: No clinically significant differences in the pharmacokinetics of the following drugs were observed when used concomitantly with JOURNAVX: oral digoxin (P-gp substrate), ethinyl estradiol (hormonal contraceptive), or levonorgestrel (hormonal contraceptive).

In Vitro Studies

Cytochrome P450 (CYP450) Enzymes: Suzetrigine inhibits CYP2C8, CYP2C9, and CYP2C19, but is not expected to result in clinically significant drug interactions. Suzetrigine does not inhibit CYP1A2, CYP2B6, CYP2D6, and CYP3A enzymes, and M6-SUZ does not inhibit CYP1A2, CYP2B6, CYP2C8, CYP2C9, CYP2C19, CYP2D6, and CYP3A enzymes. Suzetrigine induces CYP3A and to a lesser extent CYP2B6, CYP2C8, CYP2C9, and CYP2C19. Suzetrigine does not induce CYP1A2.

UDP-Glucuronosyltransferase (UGT): Suzetrigine does not inhibit UGT1A1.

Transporter Systems: Suzetrigine and M6-SUZ are not substrates of BCRP, OATP1B1 or OATP1B3. Suzetrigine is not a P-gp substrate, but M6-SUZ is a P-gp substrate. Suzetrigine inhibits OATP1B1, OATP1B3 and OAT3 but is not expected to result in clinically significant drug interactions. Suzetrigine does not inhibit BCRP, OAT1, OCT2, MATE1, and MATE2/K transporters. M6-SUZ inhibits OATP1B1, OATP1B3, OAT1, and OAT3 but is not expected to result in clinically significant drug interactions. M6-SUZ does not inhibit P-gp, BCRP, OCT2, MATE1 and MATE2/K transporters.

13 NONCLINICAL TOXICOLOGY

13.1 Carcinogenesis, Mutagenesis, Impairment of Fertility

Carcinogenesis

Long-term animal studies have not been completed to evaluate the carcinogenic potential of suzetrigine.

Mutagenesis

Suzetrigine was not mutagenic in the bacterial reverse mutation assay (Ames test), or clastogenic in the in vitro micronucleus assay with a human TK6 lymphoblastoid cell line, or in the in vivo rat bone marrow micronucleus assay.

Impairment of Fertility

In a female fertility study, female rats were treated orally with suzetrigine at 5, 10, and 15 mg/kg/day for a minimum of 14 days prior to mating, throughout mating, and through Gestation Day 7. These doses are approximately 0.57, 1.6, and 2.2-times the steady state MRHD exposure based on AUC. Increased pre-implantation loss was observed at 15 mg/kg (approximately 2.2-times the MRHD based on AUC). The finding in rats may be explained by the effect of suzetrigine on the rat progesterone receptor, which was more sensitive to suzetrigine than the human progesterone receptor based on in vitro studies. Following 4-week withdrawal of treatment, there were no effects on female fertility and early embryonic development. The finding in the rat study is of uncertain relevance to humans.

In a male fertility study, male rats were treated orally with suzetrigine at 200, 600, and 1000 mg/kg/day for a minimum of 28 days prior to mating and through mating. These doses are 3.6, 9.7, and 13.8-times the steady state MRHD exposure based on AUC, respectively. Suzetrigine had no effects on sperm parameters (motility, concentration, or morphology), reproductive performance or uterine parameters (number of implants, viable implants, pre-implantation loss, early resorptions, and post-implantation loss) at any dose.

14 CLINICAL STUDIES

14.1 Overview of Clinical Studies

The efficacy of JOURNAVX in the treatment of moderate to severe acute pain in adults was established in two randomized, double-blind, placebo and active-controlled trials of acute pain, one following full abdominoplasty (Trial 1) [see Clinical Studies (14.2)] and the other following bunionectomy (Trial 2) [see Clinical Studies (14.3)]. In each trial, pain intensity was measured using a patient-reported 11-point numeric pain rating scale (NPRS), ranging from 0 to 10, where zero corresponds to no pain and 10 corresponds to the worst pain imaginable.

Patients were eligible for study participation if they had moderate to severe pain on the verbal categorical rating system (VRS) and a pain score of ≥ 4 on the NPRS, within 4 hours of the abdominoplasty completion (Trial 1) or during the 9-hour period after discontinuation of regional anesthesia following bunionectomy (Trial 2). Once eligible, patients were randomized to receive oral JOURNAVX, placebo, or hydrocodone bitartrate/acetaminophen (HB/APAP) for a duration of 48 hours. For the JOURNAVX treatment regimen, patients received an initial loading dose of 100 mg JOURNAVX, followed by 50 mg every 12 hours. For the HB/APAP-control regimen, patients received 5 mg/325 mg every 6 hours. For both studies, 400 mg of ibuprofen every 6 hours, as needed for pain relief, was permitted as a rescue medication.

14.2 Moderate to Severe Acute Pain Following Full Abdominoplasty

Trial 1 [NCT05558410] evaluated the efficacy of JOURNAVX over 48 hours in 1,118 adult patients with moderate to severe acute pain following a full abdominoplasty procedure (JOURNAVX n = 447, placebo n = 223, and hydrocodone bitartrate/acetaminophen (HB/APAP) n = 448). The majority of patients were female (98%), and the mean age was 42 years (range: 18 to 69). The study population consisted of 70% White participants, 27% Black or African American participants, 1% Asian participants, 0.8% Native Hawaiian or other Pacific Islander participants, 0.5% American Indian or Alaska Native participants, and 0.9% Other or Multiracial participants, among which 34% identified as Hispanic or Latino. The mean pain score at baseline was 7.4 (range: 4 to 10). All baseline characteristics, including NPRS, VRS, and BMI were generally balanced across treatment arms.

In Trial 1, 89% of patients in the JOURNAVX group completed the treatment period (compared to 75% of patients in the placebo group and 85% of patients in the HB/APAP group), and 9% of patients in the JOURNAVX group discontinued due to lack of efficacy (compared to 22% of patients in the placebo group and 13% of patients in the HB/APAP group).

Efficacy was evaluated by the time-weighted sum of the pain intensity difference from 0 to 48 hours (SPID48) in the JOURNAVX group compared to the placebo group and then to the HB/APAP group. Treatment with JOURNAVX demonstrated statistically significant superior reduction in pain compared to treatment with placebo (see Table 5).

In an exploratory analysis, the time-weighted sum of the pain intensity difference from 0 to 24 hours (SPID24) reported using the least square mean was 48.0 for the JOURNAVX group and 24.2 for the placebo group. The mean pain intensities over time are depicted for the JOURNAVX, placebo, and HB/APAP groups in Figure 1.

Table 5: SPID48 Results in Adults with Moderate to Severe Acute Pain Following Full Abdominoplasty (Trial 1)
Efficacy Measure | JOURNAVX N = 447 | Placebo N = 223 | HB/APAP [HB/APAP = hydrocodone bitartrate/acetaminophen] N = 448
LS mean [A larger value of LS mean indicates better efficacy measured by SPID48.] | 118.4 | 70.1 | 111.8
LS Mean Difference vs placebo (95% CI) P value | 48.4 (33.6, 63.1) < 0.0001 | - | -
LS Mean Difference vs HB/APAP (95% CI) | 6.6 (-5.4, 18.7) | - | -
LS: Least Squares; CI: Confidence Interval

Figure 1: Mean Pain Intensity Over Time in Adults with Moderate to Severe Acute Pain Following Full Abdominoplasty (Trial 1)

Note: Pre-rescue pain scores were carried forward for 6 hours following the use of rescue medication.
HB/APAP = hydrocodone bitartrate/acetaminophen

Time to Onset of Pain Relief

The median time to meaningful pain relief (defined as a ≥ 2-point reduction in NPRS) was 119 minutes for patients in the JOURNAVX group and 480 minutes for patients in the placebo group. The median time to onset of perceptible pain relief (defined as a ≥ 1-point reduction in NPRS) for patients in the JOURNAVX group was 34 minutes.

14.3 Moderate to Severe Acute Pain Following Bunionectomy

Trial 2 [NCT05553366] evaluated the efficacy of JOURNAVX over 48 hours in 1,073 adult patients with moderate to severe acute pain following bunionectomy (JOURNAVX n = 426, placebo n = 216, and HB/APAP n = 431). The majority of patients were female (85%), and the mean age was 48 years (range: 18 to 75). The study population consisted of 71% White participants, 24% Black or African American participants, 2% Asian participants, 0.2% Native Hawaiian or other Pacific Islander participants, 1% American Indian or Alaska Native participants, and 1% Other or Multiracial participants, and 0.3% with race missing, among which 34% identified as Hispanic or Latino. The mean pain score at baseline was 6.8 (range: 4 to 10). All baseline characteristics, including NPRS, VRS, and BMI were generally balanced across treatment arms.

In Trial 2, 87% of patients in the JOURNAVX group completed the treatment period (compared to 82% of patients in the placebo group and 90% of patients in the HB/APAP group), and 12% of patients in the JOURNAVX group discontinued due to lack of efficacy (compared to 16% of patients in the placebo group and 8% of patients in the HB/APAP group).

Efficacy was evaluated by the time-weighted sum of the pain intensity difference from 0 to 48 hours (SPID48) in the JOURNAVX group compared to the placebo group and then to the HB/APAP group. Treatment with JOURNAVX demonstrated statistically significant superior reduction in pain compared to treatment with placebo (see Table 6).

In an exploratory analysis, the time-weighted sum of the pain intensity difference from 0 to 24 hours (SPID24) reported using the least square mean was 30.6 in the JOURNAVX group and 19.8 in the placebo group. The mean pain intensities over time are depicted for the JOURNAVX, placebo, and HB/APAP groups in Figure 2.

Table 6: SPID48 Results in Adults with Moderate to Severe Acute Pain Following Bunionectomy (Trial 2)
Efficacy Measure | JOURNAVX N = 426 | Placebo N = 216 | HB/APAP [HB/APAP = hydrocodone bitartrate/acetaminophen] N = 431
LS mean [A larger value of LS mean indicates better efficacy measured by SPID48.] | 99.9 | 70.6 | 120.1
LS Mean Difference vs placebo (95% CI) P value | 29.3 (14.0, 44.6) 0.0002 | - | -
LS Mean Difference vs HB/APAP (95% CI) | -20.2 (-32.7, -7.7) | - | -
LS: Least Squares; CI: Confidence Interval

Figure 2: Mean Pain Intensity Over Time in Adults with Moderate to Severe Acute Pain Following Bunionectomy (Trial 2)

Note: Pre-rescue pain scores were carried forward for 6 hours following the use of rescue medication.
HB/APAP = hydrocodone bitartrate/acetaminophen

Time to Onset of Pain Relief

The median time to meaningful pain relief (defined as ≥ 2-point reduction in NPRS) was 240 minutes for patients in the JOURNAVX group and 480 minutes in the placebo group. The median time to onset of perceptible pain relief (defined as a ≥ 1-point reduction in NPRS) for patients in the JOURNAVX group was 60 minutes.

16 HOW SUPPLIED/STORAGE AND HANDLING

JOURNAVX (suzetrigine) tablets are supplied as blue, film-coated, oblong tablets containing 50 mg of suzetrigine. Each tablet is debossed with the characters "VX50" on one side and plain on the other, and is packaged as follows:

- 30-count bottle NDC 51167-548-30
- 100-count bottle NDC 51167-548-31
- 100-count Hospital Unit Dose Carton (10 blister cards, each containing 10 tablets) NDC 51167-548-34

STORAGE AND HANDLING

Store at 68°F to 77°F (20°C to 25°C); excursions permitted to 59°F to 86°F (15°C to 30°C) [see USP Controlled Room Temperature].

17 PATIENT COUNSELING INFORMATION

Advise the patient to read the FDA-approved patient labeling (Patient Information).

Drug Interactions

Ask patients to tell you all the medications they are taking, including any herbal supplements or vitamins [see Drug Interactions (7)].

Food or drink containing grapefruit should be avoided [see Dosage and Administration (2.3), Drug Interactions (7.1)].

When used concomitantly with hormonal contraceptives containing a progestin other than levonorgestrel or norethindrone, advise patients to use an additional nonhormonal contraceptive (such as condoms) or use alternative contraceptives during JOURNAVX treatment and for 28 days after discontinuation of JOURNAVX [see Drug Interactions (7.2)].

Females of Reproductive Potential

Advise females of reproductive potential that JOURNAVX may reversibly impact the likelihood to become pregnant while on treatment. Patients using contraceptives should continue to use contraceptives [see Use in Specific Populations (8.3)].

Use in Patients with Hepatic Impairment

Inquire and/or assess whether patients have hepatic impairment.

Administration Instructions

Advise patients to take the starting dose of JOURNAVX on an empty stomach at least 1 hour before or 2 hours after food to avoid delay in onset of action. Clear liquids may be consumed (such as water, apple juice, vegetable broth, tea, or black coffee) during this time. Avoid food or drink containing grapefruit during treatment with JOURNAVX [see Dosage and Administration (2.2, 2.3)].

Subsequent doses of JOURNAVX can be taken with or without food.

Patients should be instructed to swallow JOURNAVX tablets whole (do not chew or crush).

Inform patients about what to do in the event they miss a dose of JOURNAVX [see Dosage and Administration (2.4)].

Manufactured for: Vertex Pharmaceuticals Incorporated; 50 Northern Avenue, Boston, MA 02210
JOURNAVX, VERTEX and associated logos are registered trademarks of Vertex Pharmaceuticals Incorporated.
©2026 Vertex Pharmaceuticals Incorporated

PATIENT INFORMATION
JOURNAVX (jor na vix)
(suzetrigine)
tablets, for oral use

What is JOURNAVX?
JOURNAVX is a prescription medicine used to treat adults with moderate to severe short-term (acute) pain, including postoperative pain.
It is not known if JOURNAVX is safe and effective in children.

Do not take JOURNAVX if you take certain medicines that are strong inhibitors of an enzyme called CYP3A.
Ask your healthcare provider if you are not sure.

Before taking JOURNAVX, tell your healthcare provider about all of your medical conditions, including if you:

- have liver problems. People with liver problems may have an increased risk of getting side effects from taking JOURNAVX.
- are pregnant or plan to become pregnant. It is not known if JOURNAVX will harm your unborn baby. You and your healthcare provider should decide if you will take JOURNAVX while you are pregnant.
- are breastfeeding or planning to breastfeed. It is not known if JOURNAVX passes into your breast milk. You and your healthcare provider should decide if you will take JOURNAVX while you are breastfeeding.

Tell your healthcare provider about all the medicines you take, including prescription and over-the-counter medicines, vitamins, and herbal supplements.
Taking JOURNAVX with certain other medicines may affect the way JOURNAVX and the other medicines work and may increase your risk of side effects. See "Do not take JOURNAVX". Ask your healthcare provider or pharmacist for a list of these medicines if you are not sure.
Especially tell your healthcare provider if you take:

- hormonal birth control (contraceptives) containing progestins other than levonorgestrel or norethindrone. If you take one of these contraceptives (progestins other than levonorgestrel or norethindrone), they may not work as well during treatment with JOURNAVX. You should also use nonhormonal contraceptives such as condoms or use other forms of hormonal birth control during treatment with JOURNAVX and for 28 days after you stop taking JOURNAVX.
- medicines that are substrates of the CYP3A enzyme since they may become less effective during treatment with JOURNAVX. Your healthcare provider may need to adjust the dose of your medicine when starting or stopping JOURNAVX.

Know the medicines you take. Keep a list of them to show your healthcare provider and pharmacist when you get a new medicine.

How should I take JOURNAVX?

- Take JOURNAVX by mouth exactly as your healthcare provider tells you to take it.
- Swallow JOURNAVX tablets whole. Do not chew or crush the tablets.
- For your first dose of JOURNAVX:
  - Take 2 JOURNAVX tablets on an empty stomach.
  - Take your first dose of JOURNAVX at least 1 hour before or 2 hours after food. During this time, you may drink clear liquids, such as water, apple juice, vegetable broth, tea, or black coffee.
- After your first dose of JOURNAVX:
  - Take 1 JOURNAVX tablet 12 hours later, with or without food.
  - Continue to take 1 JOURNAVX tablet every 12 hours as directed by your healthcare provider.
- Take JOURNAVX for the shortest time needed.
- If you have liver problems or take certain other medicines, your dosing schedule may be different.
- If you miss a dose of JOURNAVX and do not have liver problems or take certain other medicines:
  - Take the missed dose as soon as possible, then take your next scheduled dose at your recommended time.
  - If you miss 2 or more doses of JOURNAVX, take 2 JOURNAVX tablets, then take your next scheduled dose at your recommended time.
- If you miss a dose of JOURNAVX and you have liver problems or are taking moderate inhibitors of an enzyme called CYP3A:
  - Take the missed dose as soon as possible.
  - If you took the missed dose and your next scheduled dose is within 6 hours, skip that dose and take your next scheduled dose at your recommended time.
- If you are not sure about your dosing, ask your healthcare provider or pharmacist.
- If you take too much JOURNAVX, call your healthcare provider or Poison Help line at 1-800-222-1222 or go to the nearest hospital emergency room right away.

What should I avoid while taking JOURNAVX?

- Do not take food or drink containing grapefruit during treatment with JOURNAVX.

What are possible side effects of JOURNAVX?
The most common side effects of JOURNAVX include:

- itching
- muscle spasms
- increased blood level of creatine phosphokinase
- rash

JOURNAVX may temporarily reduce the chance of females becoming pregnant while on treatment. Talk to your healthcare provider if you have concerns about becoming pregnant. If you are using contraceptives, you should continue to use contraceptives during treatment with JOURNAVX.
Tell your healthcare provider if you have any side effect that bothers you or that does not go away.
These are not all of the possible side effects of JOURNAVX.
Call your doctor for medical advice about side effects. You may report side effects to FDA at 1-800-FDA-1088.

How should I store JOURNAVX?
Store JOURNAVX at room temperature between 68°F to 77°F (20°C to 25°C).
Keep JOURNAVX and all medicines out of the reach of children.

General information about the safe and effective use of JOURNAVX.
Medicines are sometimes prescribed for purposes other than those listed in a Patient Information Leaflet. Do not use JOURNAVX for a condition for which it was not prescribed. Do not give JOURNAVX to other people, even if they have the same symptoms that you have. It may harm them. You can ask your pharmacist or healthcare provider for information about JOURNAVX that is written for health professionals.

What are the ingredients in JOURNAVX?
Active ingredient: suzetrigine
Inactive ingredients: croscarmellose sodium, hypromellose acetate succinate, magnesium stearate, and microcrystalline cellulose. The tablet film coat contains FD&C Blue #2 aluminum lake, polyethylene glycol, polyvinyl alcohol-partially hydrolyzed, talc, and titanium dioxide.
Manufactured for: Vertex Pharmaceuticals Incorporated; 50 Northern Avenue, Boston, MA 02210
JOURNAVX, VERTEX and associated logos are registered trademarks of Vertex Pharmaceuticals Incorporated.
©2026 Vertex Pharmaceuticals Incorporated
For more information, go to www.JOURNAVX.com or call 1-877-634-8789.

This Patient Information has been approved by the U.S. Food and Drug Administration.

Issued: 01/2026

PRINCIPAL DISPLAY PANEL - 50 mg Tablet Bottle Label

Rx Only

NDC 51167-548-30

JOURNAVX™
(suzetrigine) tablets

50 mg

Contains: 30 tablets
For Oral Use

Recommended Dosage:
See Prescribing Information.

PRINCIPAL DISPLAY PANEL - 50 mg Tablet Bottle Label - NDC 51167-548-31

Rx Only

NDC 51167-548-31

JOURNAVX™
(suzetrigine) tablets

50 mg

Contains: 100 tablets
For Oral Use

Recommended Dosage:
See Prescribing Information.

PRINCIPAL DISPLAY PANEL - 50 mg Tablet Blister Pack Carton

For institutional use only

NDC 51167-548-34
Rx Only

JOURNAVX™
(suzetrigine) tablets

50 mg

100 tablets

UNIT DOSE

PRINCIPAL DISPLAY PANEL - 50 mg Tablet Blister Pack Carton - Professional Sample

PROFESSIONAL SAMPLE - NOT FOR SALE

NDC 51167-548-25
Rx Only

JOURNAVX™
(suzetrigine) tablets

50 mg per tablet

For Oral Use

Contains:
5 blister wallets
with 5 tablets each